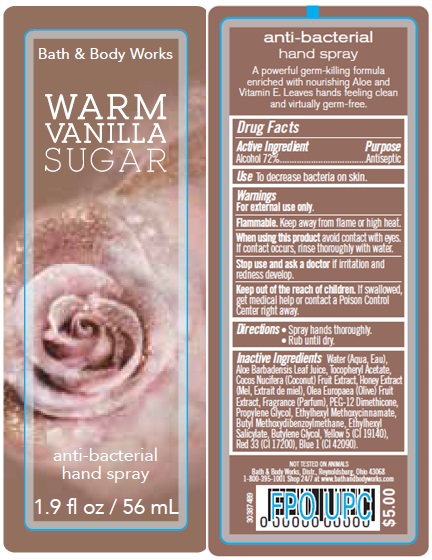 DRUG LABEL: Anti-Bacterial Hand
NDC: 62670-5023 | Form: SPRAY
Manufacturer: Bath & Body Works, Inc.
Category: otc | Type: HUMAN OTC DRUG LABEL
Date: 20160105

ACTIVE INGREDIENTS: ALCOHOL 72 mL/100 mL
INACTIVE INGREDIENTS: WATER

ACTIVE INGREDIENT

Alcohol (72%)

PURPOSE

Antiseptic

USE

To decrease bacteria on skin.

WARNINGS

For external use only.

WHEN USING THIS PRODUCT

avoid contact with eyes.

STOP USE AND ASK A DOCTOR

if irritation and redness develop.

FLAMMABLE

Keep away from flame or high heat.

KEEP OUT OF REACH OF CHILDREN

If swallowed, get medical help or contact a Poison Control Center right away.

DIRECTIONS

- Spray hands thoroughly.
- Rub until dry.

INACTIVE INGREDIENTS

Water (Aqua, Eau), Aloe Barbadensis Leaf Juice, Tocopheryl Acetate, Cocos Nucifera (Coconut) Fruit Extract, Honey Extract (Mel, Extrait de miel), Olea Europaea (Olive) Fruit Extract, Fragrance (Parfum), PEG-12 Dimethicone, Propylene Glycol, Ethylhexyl Methoxycinnamate, Butyl Methoxydibenzoylmethane, Ethylhexyl Salicylate, Butylene Glycol, Yellow 5 (CI 19140), Red 33 (CI 17200), Blue 1 (CI 42090).

COMPANY INFORMATION

Bath & Body Works, Distr.

Reynoldsburg, Ohio 43068

1-800-395-1001

www.bathandbodyworks.com